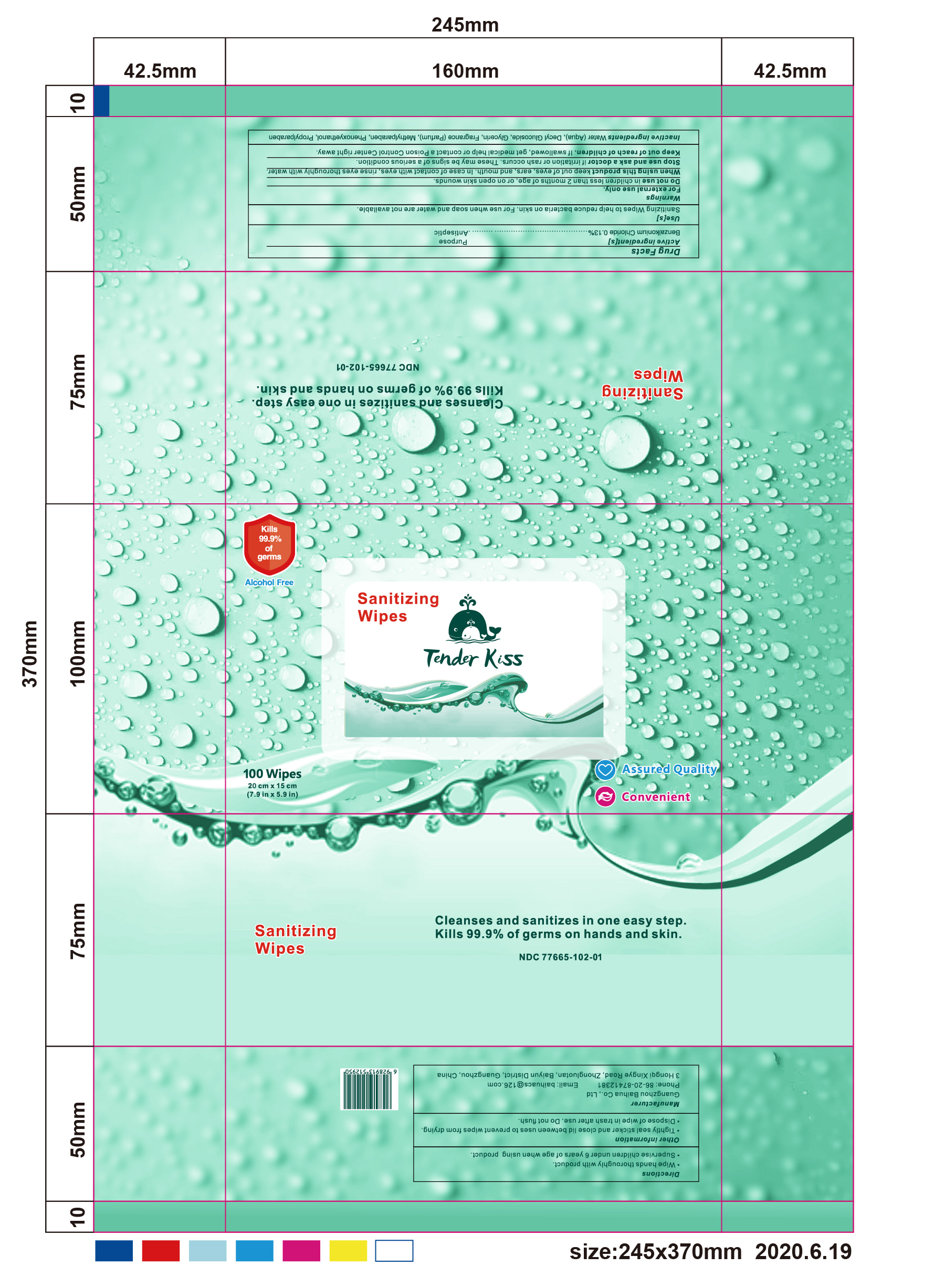 DRUG LABEL: Sanitizing Wipes
NDC: 77665-102 | Form: CLOTH
Manufacturer: Guangzhou Baihua Co., Ltd
Category: otc | Type: HUMAN OTC DRUG LABEL
Date: 20211216

ACTIVE INGREDIENTS: BENZALKONIUM CHLORIDE 0.13 g/100 g
INACTIVE INGREDIENTS: PHENOXYETHANOL 1 g/100 g; METHYLPARABEN 0.1 g/100 g; PROPYLPARABEN 0.1 g/100 g; GLYCERIN 2 g/100 g; DECYL GLUCOSIDE 1 g/100 g; WATER; FRAGRANCE LAVENDER & CHIA F-153480 0.03 g/100 g

Sanitizing Wipes

Sanitizing Wipes

This is a sanitizing wipe product manufactured using only the following United States Pharmacopoeia (USP) grade ingredients in the preparation of the product:

1. Benzalkonium Chloride (0.13%)
2. RO pure water
3. Decyl Glucoside (1%)
4. Glycerin (2%)
5. Fragrance (Parfum) (0.03%)
6. Methylparaben (0.1%)
7. Phenoxyethanol (1%)
8. Propylparaben (0.1%)

Active Ingredient(s)

Benzalkonium Chloride 0.13%. Purpose: Antiseptic

Purpose

Antiseptic, Sanitizing Wipes

Use

Sanitizing Wipes to help reduce bacteria on skin. For use when soap and water are not available.

Warnings

For external use only.

Do not use

- in children less than 2 months of age
- on open skin wounds

When using this product keep out of eyes, ears, and mouth. In case of contact with eyes, rinse eyes thoroughly with water.
Stop use and ask a doctor if irritation or rash occurs. These may be signs of a serious condition.
Keep out of reach of children. If swallowed, get medical help or contact a Poison Control Center right away.

Stop use and ask a doctor if irritation or rash occurs. These may be signs of a serious condition.

Keep out of reach of children. If swallowed, get medical help or contact a Poison Control Center right away.

Directions

- Wipe hands thoroughly with product.
- Supervise children under 6 years of age when using product.

Inactive ingredients

Water (Aqua), Decyl Glucoside, Glycerin, Fragrance (Parfum), Methylparaben, Phenoxyethanol, Propylparaben

Package Label - Principal Display Panel

100 mL NDC: 77665-102-01